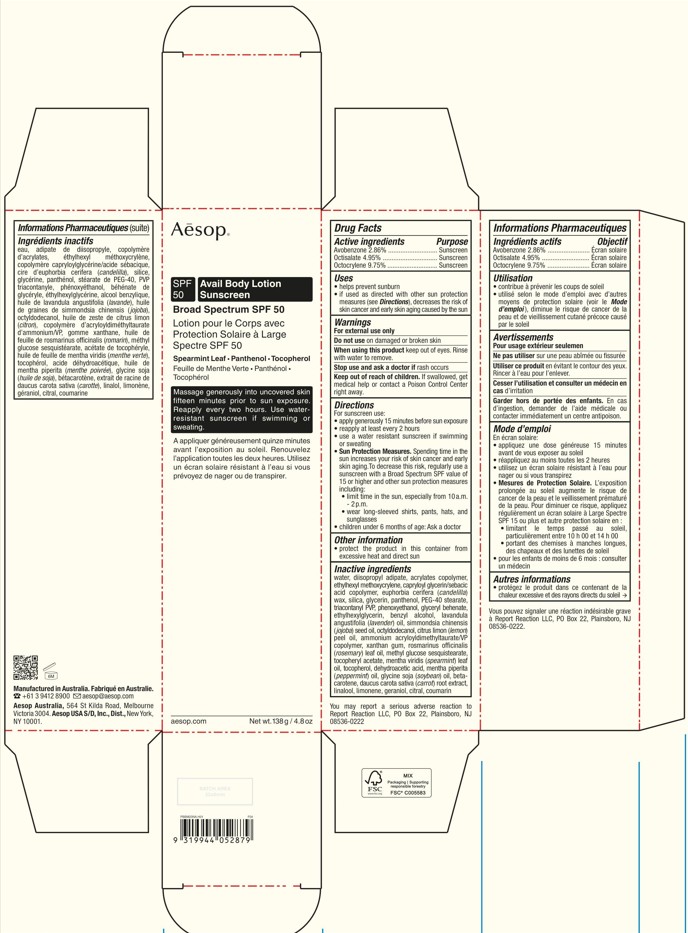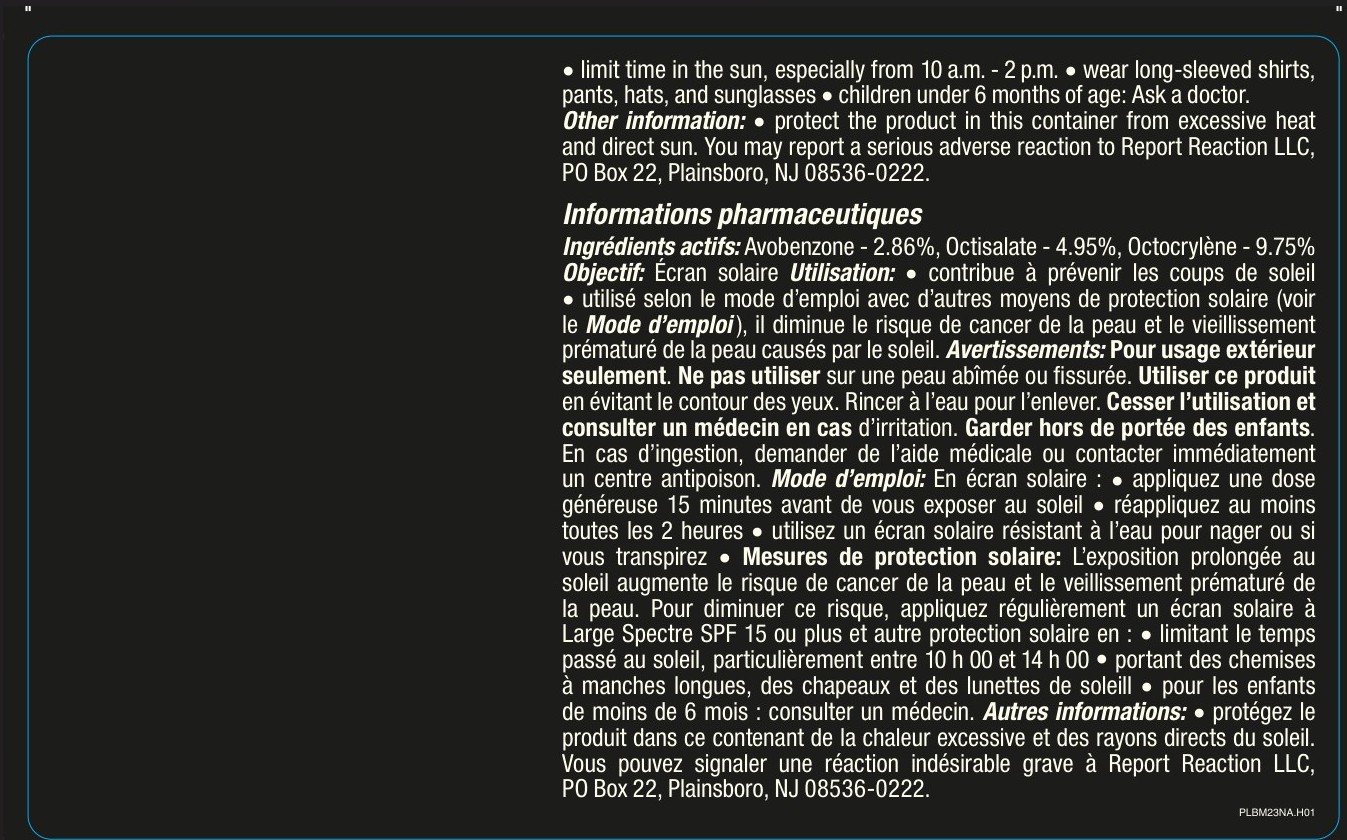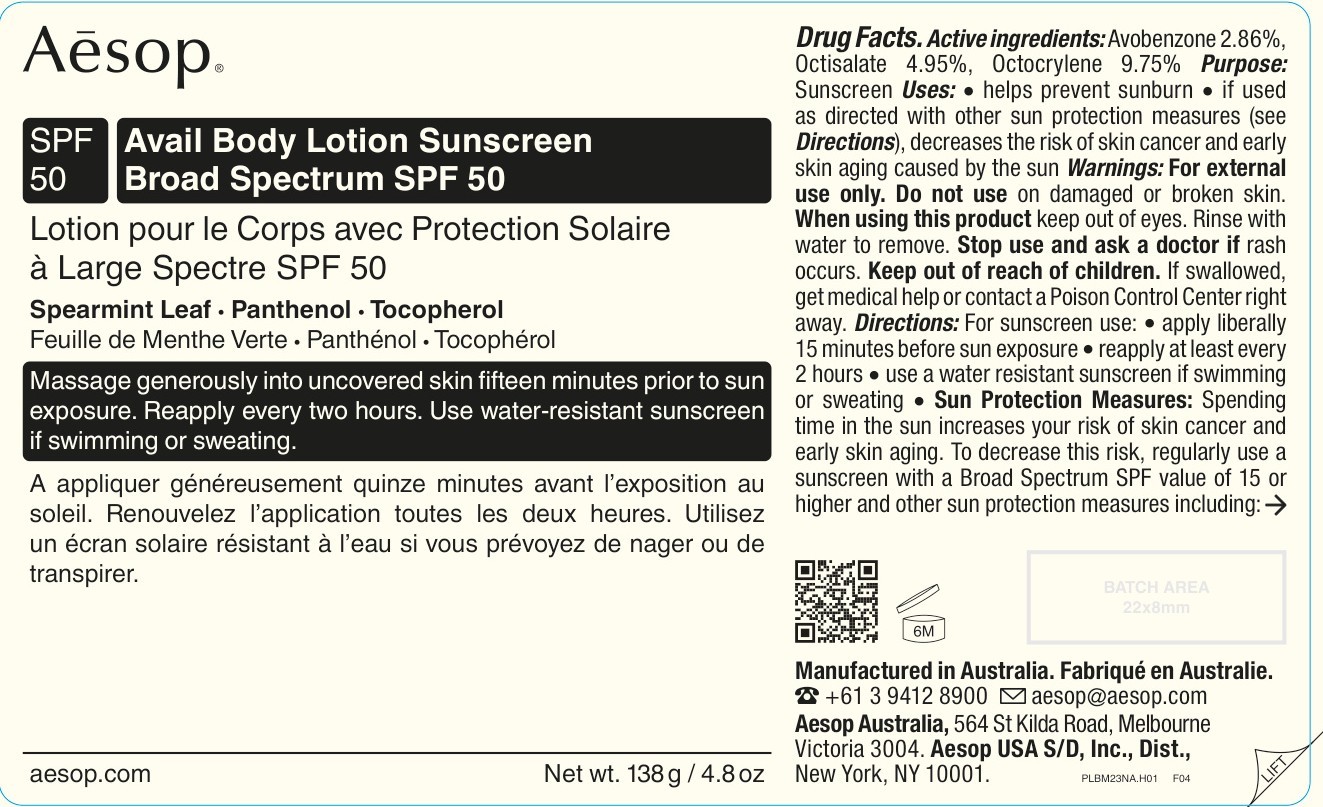 DRUG LABEL: AESOP Avail Body Sunscreen Broad Spectrum SPF 50
NDC: 76293-879 | Form: LOTION
Manufacturer: Emeis Cosmetics Pty Ltd
Category: otc | Type: HUMAN OTC DRUG LABEL
Date: 20251017

ACTIVE INGREDIENTS: AVOBENZONE 28.6 mg/1 g; OCTISALATE 49.5 mg/1 g; OCTOCRYLENE 97.5 mg/1 g
INACTIVE INGREDIENTS: WATER; DIISOPROPYL ADIPATE; ETHYLHEXYL METHOXYCRYLENE; CAPRYLOYL GLYCERIN/SEBACIC ACID COPOLYMER (2000 MPA.S); EUPHORBIA CERIFERA (CANDELILLA) WAX; SILICA; GLYCERIN; PANTHENOL; PEG-40 STEARATE; TRIACONTANYL PVP; PHENOXYETHANOL; GLYCERYL BEHENATE/EICOSADIOATE; ETHYLHEXYLGLYCERIN; BENZYL ALCOHOL; LAVANDULA ANGUSTIFOLIA (LAVENDER) OIL; SIMMONDSIA CHINENSIS (JOJOBA) SEED OIL; OCTYLDODECANOL; CITRUS LIMON (LEMON) PEEL OIL; AMMONIUM ACRYLOYLDIMETHYLTAURATE/VP COPOLYMER; XANTHAN GUM; ROSMARINUS OFFICINALIS (ROSEMARY) LEAF OIL; METHYL GLUCOSE SESQUISTEARATE; .ALPHA.-TOCOPHEROL ACETATE, D-; MENTHA VIRIDIS (SPEARMINT) LEAF OIL; TOCOPHEROL; DEHYDROACETIC ACID; MENTHA PIPERITA (PEPPERMINT) OIL; SOYBEAN OIL; BETA-CAROTENE; CARROT; LINALOOL; LIMONENE, (+)-; GERANIOL; CITRAL; COUMARIN

Drug Facts

Active ingredients

Avobenzone 2.86%
Octisalate 4.95%
Octocrylene 9.75%

Purpose

Sunscreen

Uses

- helps prevent sunburn.
- if used as directed with other sun protection measures (see Directions), decreases the risk of skin cancer and early skin aging caused by the sun.

Warnings

For external use only.

Do not use

on damaged or broken skin.

When using this product

keep out of eyes. Rinse with water to remove.

Stop use and ask a doctor

if rash occurs.

Keep out of reach of children.

If swallowed, get medical help or contact a Poison Control Center right away.

Directions

For sunscreen use:

- Apply generously 15 minutes before sun exposure.
- reapply at least every 2 hours
- use a water resistant sunscreen if swimming or sweating

- Sun Protection Measures. Spending time in the sun increases your risk of skin cancer and early

skin aging.To decrease this risk, regularly use a
sunscreen with a Broad Spectrum SPF value of
15 or higher and other sun protection measures
including:
• limit time in the sun, especially from 10 a.m.
- 2 p.m.
• wear long-sleeved shirts, pants, hats, and
sunglasses
• children under 6 months of age: Ask a doctor

Other information

- Protect the product in this container from excessive heat and direct sun.
- You may report a serious adverse reaction to Report Reaction LLC, PO Box 22, Plainsboro, NJ 08536-0222.

Inactive ingredients

water, diisopropyl adipate, acrylates copolymer,
ethylhexyl methoxycrylene, capryloyl glycerin/sebacic
acid copolymer, euphorbia cerifera (candelilla)
wax, silica, glycerin, panthenol, PEG-40 stearate,
triacontanyl PVP, phenoxyethanol, glyceryl behenate,
ethylhexylglycerin, benzyl alcohol, lavandula
angustifolia (lavender) oil, simmondsia chinensis
(jojoba) seed oil, octyldodecanol, citrus limon (lemon)
peel oil, ammonium acryloyldimethyltaurate/VP
copolymer, xanthan gum, rosmarinus officinalis
(rosemary) leaf oil, methyl glucose sesquistearate,
tocopheryl acetate, mentha viridis (spearmint) leaf
oil, tocopherol, dehydroacetic acid, mentha piperita
(peppermint) oil, glycine soja (soybean) oil, beta-carotene, daucus carota sativa (carrot) root extract,
linalool, limonene, geraniol, citral, coumarin